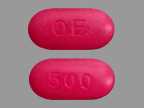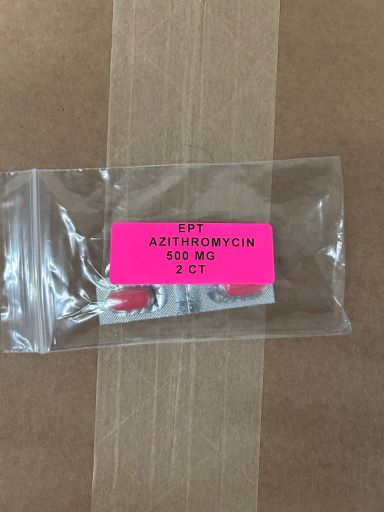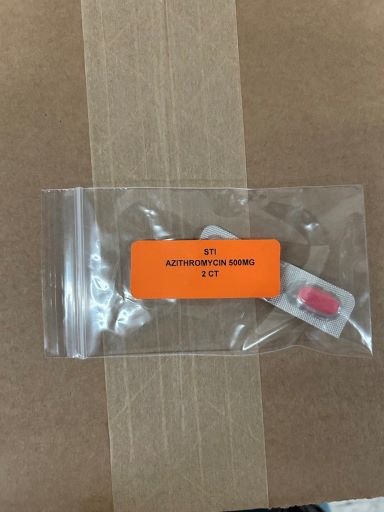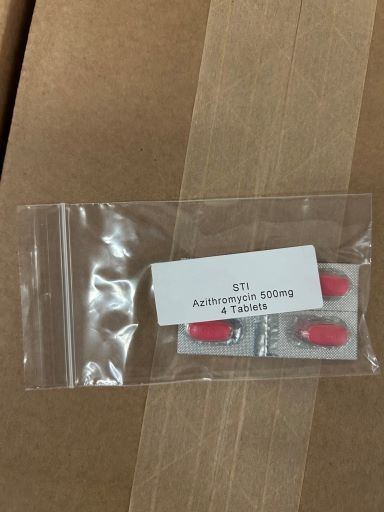 DRUG LABEL: Azithromycin Dihydrate
NDC: 83112-501 | Form: TABLET, FILM COATED
Manufacturer: Health Department, Oklahoma State
Category: prescription | Type: HUMAN PRESCRIPTION DRUG LABEL
Date: 20251231

ACTIVE INGREDIENTS: AZITHROMYCIN DIHYDRATE 500 mg/1 1

Azithromycin 500mg

INDICATIONS AND USAGE

Azithromycin is a macrolide antibacterial drug indicated for the treatment of patients with mild to moderate infections caused by susceptible strains of the designated microorganisms in the specific conditions listed below. Recommended dosages and durations of therapy in adult and pediatric patient populations vary in these indications. [see Dosage and Administration (2)]

1.1 Adult Patients

Acute bacterial exacerbations of chronic bronchitis due to Haemophilus influenzae, Moraxella catarrhalis, or Streptococcus pneumoniae.
Acute bacterial sinusitis due to Haemophilus influenzae, Moraxella catarrhalis. or Streptococcus pneumoniae.
Community-acquired pneumonia due to Chlamydophila pneumoniae, Haemophilus influenzae, Mycoplasma pneumoniae, or Streptococcus pneumoniae in patients appropriate for oral therapy.
Pharyngitis/tonsillitis caused by Streptococcus pyogenes as an alternative to first-line therapy in individuals who cannot use first-line therapy.
Uncomplicated skin and skin structure infections due to Staphylococcus aureus, Streptococcus pyogenes, or Streptococcus agalactiae.
Urethritis and cervicitis due to Chlamydia trachomatis or Neisseria gonorrhoeae.
Genital ulcer disease in men due to Haemophilus ducreyi (chancroid). Due to the small number of women included in clinical trials, the efficacy of azithromycin in the treatment of chancroid in women has not been established.

1.2 Pediatric Patients

[see Use in Specific Populations (8.4) and Clinical Studies (14.2)]

Acute otitis media (> 6 months of age) caused by Haemophilus influenzae, Moraxella catarrhalis, or Streptococcus pneumoniae
Community-acquired pneumonia (> 6 months of age) due to Chlamydophila pneumoniae, Haemophilus influenzae, Mycoplasma pneumonia, or Streptococcus pneumoniae in patients appropriate for oral therapy.
Pharyngitis/tonsillitis (> 2 years of age) caused by Streptococcus pyogenes as an alternative to first-line therapy in individuals who cannot use first-line therapy.

1.3 Limitations of Use

Azithromycin should not be used in patients with pneumonia who are judged to be inappropriate for oral therapy because of moderate to severe illness or risk factors such as any of the following:

patients with cystic fibrosis,
patients with nosocomial infections,
patients with known or suspected bacteremia,
patients requiring hospitalization,
elderly or debilitated patients, or
patients with significant underlying health problems that may compromise their ability to respond to their illness (including immunodeficiency or functional asplenia).

1.4 Usage

To reduce the development of drug-resistant bacteria and maintain the effectiveness of azithromycin and other antibacterial drugs, azithromycin should be used only to treat infections that are proven or strongly suspected to be caused by susceptible bacteria. When culture and susceptibility information are available, they should be considered in selecting or modifying antibacterial therapy. In the absence of such data, local epidemiology and susceptibility patterns may contribute to the empiric selection of therapy.

DOSAGE AND ADMINISTRATION

2.1 Adult Patients

[see Indications and Usage (1.1) and Clinical Pharmacology (12.3)]

Infection* Recommended Dose/Duration of Therapy

*
DUE TO THE INDICATED ORGANISMS [see Indications and Usage (1.1)]

Community-acquired pneumonia
Pharyngitis/tonsillitis (second-line therapy)
Skin/skin structure (uncomplicated) 500 mg as a single dose on Day 1, followed by 250 mg once daily on Days 2 through 5
Acute bacterial exacerbations of chronic obstructive pulmonary disease 500 mg once daily for 3 days
OR
500 mg as a single dose on Day 1, followed by 250 mg once daily on Days 2 through 5
Acute bacterial sinusitis 500 mg once daily for 3 days
Genital ulcer disease (chancroid) One single 1 gram dose
Non-gonococcal urethritis and cervicitis One single 1 gram dose
Gonococcal urethritis and cervicitis One single 2 gram dose

Azithromycin tablets can be taken with or without food.

2.2 Pediatric Patients1

Infection* Recommended Dose/Duration of Therapy
1 see dosing tables below for maximum doses evaluated by indication

*
DUE TO THE INDICATED ORGANISMS [see Indications and Usage (1.2)]

Acute otitis media 30 mg/kg as a single dose or 10 mg/kg once daily for 3 days or 10 mg/kg as a single dose on Day 1 followed by 5 mg/kg/day on Days 2 through 5
Acute bacterial sinusitis 10 mg/kg once daily for 3 days
Community-acquired pneumonia 10 mg/kg as a single dose on Day 1 followed by 5 mg/kg once daily on Days 2 through 5
Pharyngitis/tonsillitis 12 mg/kg once daily for 5 days

Azithromycin for oral suspension can be taken with or without food.

PEDIATRIC DOSAGE GUIDELINES FOR OTITIS MEDIA, ACUTE BACTERIAL SINUSITIS, AND COMMUNITY-ACQUIRED PNEUMONIA

(Age 6 months and above, [see Use in Specific Populations (8.4)])

Based on Body Weight

OTITIS MEDIA AND COMMUNITY-ACQUIRED PNEUMONIA: (5-Day Regimen)*
Dosing Calculated on 10 mg/kg/day Day 1 and 5 mg/kg/day Days 2 to 5.
Weight 100 mg/5 mL 200 mg/5 mL Total mL per Treatment Course Total mg per Treatment Course
Kg Day 1 Days 2 to 5 Day 1 Days 2 to 5

*
Effectiveness of the 3-day or 1-day regimen in pediatric patients with community-acquired pneumonia has not been established.

5 2.5 mL; (½ tsp) 1.25mL; (¼ tsp) 7.5 mL 150 mg
10 5 mL; (1 tsp) 2.5 mL; (½ tsp) 15 mL 300 mg
20 5 mL; (1 tsp) 2.5 mL; (½ tsp) 15 mL 600 mg
30 7.5 mL; (1½ tsp) 3.75 mL; (¾ tsp) 22.5 mL 900 mg
40 10 mL; (2 tsp) 5 mL; (1 tsp) 30 mL 1,200 mg
50 and above 12.5 mL; (2½ tsp) 6.25 mL; (1¼ tsp) 37.5 mL 1,500 mg

OTITIS MEDIA AND ACUTE BACTERIAL SINUSITIS: (3-Day Regimen)*
Dosing Calculated on 10 mg/kg/day.
Weight 100 mg/5 mL 200 mg/5 mL Total mL per Treatment Course Total mg per Treatment Course
Kg Days 1 to 3 Days 1 to 3

*
Effectiveness of the 5-day or 1-day regimen in pediatric patients with acute bacterial sinusitis has not been established.

5 2.5 mL; (½ tsp) 7.5 mL 150 mg
10 5 mL; (1 tsp) 15 mL 300 mg
20 5 mL; (1 tsp) 15 mL 600 mg
30 7.5 mL; (1½ tsp) 22.5 mL 900 mg
40 10 mL; (2 tsp) 30 mL 1,200 mg
50 and above 12.5 mL; (2½ tsp) 37.5 mL 1,500 mg

OTITIS MEDIA: (1-Day Regimen)
Dosing Calculated on 30 mg/kg as a single dose.
Weight 200 mg/5 mL Total mL per Treatment Course Total mg per Treatment Course
Kg 1-Day Regimen
5 3.75 mL; (3/4 tsp) 3.75 mL 150 mg
10 7.5 mL; (1½ tsp) 7.5 mL 300 mg
20 15 mL; (3 tsp) 15 mL 600 mg
30 22.5 mL; (4½ tsp) 22.5 mL 900 mg
40 30 mL; (6 tsp) 30 mL 1,200 mg
50 and above 37.5 mL; (7½ tsp) 37.5 mL 1,500 mg

The safety of re-dosing azithromycin in pediatric patients who vomit after receiving 30 mg/kg as a single dose has not been established. In clinical studies involving 487 patients with acute otitis media given a single 30 mg/kg dose of azithromycin, 8 patients who vomited within 30 minutes of dosing were re-dosed at the same total dose.

Pharyngitis/Tonsillitis: The recommended dose of azithromycin for children with pharyngitis/tonsillitis is 12 mg/kg once daily for 5 days. (See chart below.)

PEDIATRIC DOSAGE GUIDELINES FOR PHARYNGITIS/TONSILLITIS

(Age 2 years and above, [see Use in Specific Populations (8.4)])

Based on Body Weight

PHARYNGITIS/TONSILLITIS: (5-Day Regimen)
Dosing Calculated on 12 mg/kg/day for 5 days.
Weight 200 mg/5 mL Total mL per Treatment Course Total mg per Treatment Course
Kg Days 1 to 5
8 2.5 mL; (½ tsp) 12.5 mL 500 mg
17 5 mL; (1 tsp) 25 mL 1,000 mg
25 7.5 mL; (1½ tsp) 37.5 mL 1,500 mg
33 10 mL; (2 tsp) 50 mL 2,000 mg
40 12.5 mL; (2½ tsp) 62.5 mL 2,500 mg

DOSAGE FORMS AND STRENGTHS

Azithromycin Tablets USP, 500 mg (debossed "OE" on one side and "500" on the other side) are supplied as red, oval, film coated tablets containing azithromycin dihydrate equivalent to 500 mg azithromycin.

CONTRAINDICATIONS

4.1 Hypersensitivity

Azithromycin is contraindicated in patients with known hypersensitivity to azithromycin, erythromycin, any macrolide, or ketolide drug.

4.2 Hepatic Dysfunction

Azithromycin is contraindicated in patients with a history of cholestatic jaundice/hepatic dysfunction associated with prior use of azithromycin.

WARNINGS AND PRECAUTIONS

5.1 Hypersensitivity

Serious allergic reactions, including angioedema, anaphylaxis, and dermatologic reactions including Acute Generalized Exanthematous Pustulosis (AGEP), Stevens-Johnson syndrome, and toxic epidermal necrolysis have been reported in patients on azithromycin therapy. [see Contraindications (4.1)]

Fatalities have been reported. Cases of Drug Reaction with Eosinophilia and Systemic Symptoms (DRESS) have also been reported. Despite initially successful symptomatic treatment of the allergic symptoms, when symptomatic therapy was discontinued, the allergic symptoms recurred soon thereafter in some patients without further azithromycin exposure. These patients required prolonged periods of observation and symptomatic treatment. The relationship of these episodes to the long tissue half-life of azithromycin and subsequent prolonged exposure to antigen is presently unknown.

If an allergic reaction occurs, the drug should be discontinued and appropriate therapy should be instituted. Physicians should be aware that allergic symptoms may reappear when symptomatic therapy has been discontinued.

5.2 Hepatotoxicity

Abnormal liver function, hepatitis, cholestatic jaundice, hepatic necrosis, and hepatic failure have been reported, some of which have resulted in death. Discontinue azithromycin immediately if signs and symptoms of hepatitis occur.

5.3 Infantile Hypertrophic Pyloric Stenosis (IHPS)

Following the use of azithromycin in neonates (treatment up to 42 days of life), IHPS has been reported. Direct parents and caregivers to contact their physician if vomiting or irritability with feeding occurs.

5.4 QT Prolongation

Prolonged cardiac repolarization and QT interval, imparting a risk of developing cardiac arrhythmia and torsades de pointes, have been seen with treatment with macrolides, including azithromycin. Cases of torsades de pointes have been spontaneously reported during postmarketing surveillance in patients receiving azithromycin. Providers should consider the risk of QT prolongation which can be fatal when weighing the risks and benefits of azithromycin for at-risk groups including:

patients with known prolongation of the QT interval, a history of torsades de pointes, congenital long QT syndrome, bradyarrhythmias or uncompensated heart failure
patients on drugs known to prolong the QT interval
patients with ongoing proarrhythmic conditions such as uncorrected hypokalemia or hypomagnesemia, clinically significant bradycardia, and in patients receiving Class IA (quinidine, procainamide) or Class III (dofetilide, amiodarone, sotalol) antiarrhythmic agents.

Elderly patients may be more susceptible to drug-associated effects on the QT interval.

5.5 Clostridium difficile-Associated Diarrhea (CDAD)

Clostridium difficile-associated diarrhea has been reported with use of nearly all antibacterial agents, including azithromycin, and may range in severity from mild diarrhea to fatal colitis. Treatment with antibacterial agents alters the normal flora of the colon, leading to overgrowth of C. difficile.

C. difficile produces toxins A and B which contribute to the development of CDAD. Hypertoxin producing strains of C. difficile cause increased morbidity and mortality, as these infections can be refractory to antibacterial therapy and may require colectomy. CDAD must be considered in all patients who present with diarrhea following antibiotic use. Careful medical history is necessary since CDAD has been reported to occur over two months after the administration of antibacterial agents.

If CDAD is suspected or confirmed, ongoing antibiotic use not directed against C. difficile may need to be discontinued. Appropriate fluid and electrolyte management, protein supplementation, antibiotic treatment of C. difficile, and surgical evaluation should be instituted as clinically indicated.

5.6 Exacerbation of Myasthenia Gravis

Exacerbation of symptoms of myasthenia gravis and new onset of myasthenic syndrome have been reported in patients receiving azithromycin therapy.

5.7 Use in Sexually Transmitted Infections

Azithromycin, at the recommended dose, should not be relied upon to treat syphilis. Antibacterial agents used to treat non-gonococcal urethritis may mask or delay the symptoms of incubating syphilis. All patients with sexually transmitted urethritis or cervicitis should have a serologic test for syphilis and appropriate testing for gonorrhea performed at the time of diagnosis. Appropriate antibacterial therapy and follow-up tests for these diseases should be initiated if infection is confirmed.

5.8 Development of Drug-Resistant Bacteria

Prescribing azithromycin in the absence of a proven or strongly suspected bacterial infection is unlikely to provide benefit to the patient and increases the risk of the development of drug-resistant bacteria.

ADVERSE REACTIONS

6.1 Clinical Trials Experience

Because clinical trials are conducted under widely varying conditions, adverse reaction rates observed in the clinical trials of a drug cannot be directly compared to rates in the clinical trials of another drug and may not reflect the rates observed in practice.

In clinical trials, most of the reported side effects were mild to moderate in severity and were reversible upon discontinuation of the drug. Potentially serious adverse reactions of angioedema and cholestatic jaundice were reported. Approximately 0.7% of the patients (adults and pediatric patients) from the 5-day multiple-dose clinical trials discontinued azithromycin therapy because of treatment-related adverse reactions. In adults given 500 mg/day for 3 days, the discontinuation rate due to treatment-related adverse reactions was 0.6%. In clinical trials in pediatric patients given 30 mg/kg, either as a single dose or over 3 days, discontinuation from the trials due to treatment-related adverse reactions was approximately 1%. Most of the adverse reactions leading to discontinuation were related to the gastrointestinal tract, e.g., nausea, vomiting, diarrhea, or abdominal pain. [see Clinical Studies (14.2)]

Adults

Multiple-dose regimens: Overall, the most common treatment-related adverse reactions in adult patients receiving multiple-dose regimens of azithromycin were related to the gastrointestinal system with diarrhea/loose stools (4% to 5%), nausea (3%), and abdominal pain (2% to 3%) being the most frequently reported.

No other adverse reactions occurred in patients on the multiple-dose regimens of azithromycin with a frequency greater than 1%. Adverse reactions that occurred with a frequency of 1% or less included the following:

Cardiovascular: Palpitations, chest pain.
Gastrointestinal: Dyspepsia, flatulence, vomiting, melena, and cholestatic jaundice.
Genitourinary: Monilia, vaginitis, and nephritis.
Nervous System: Dizziness, headache, vertigo, and somnolence.
General: Fatigue.
Allergic: Rash, pruritus, photosensitivity, and angioedema.

Single 1-gram dose regimen:

Overall, the most common adverse reactions in patients receiving a single-dose regimen of 1 gram of azithromycin were related to the gastrointestinal system and were more frequently reported than in patients receiving the multiple-dose regimen.

Adverse reactions that occurred in patients on the single 1-gram dosing regimen of azithromycin with a frequency of 1% or greater included diarrhea/loose stools (7%), nausea (5%), abdominal pain (5%), vomiting (2%), dyspepsia (1%), and vaginitis (1%).

Single 2-gram dose regimen:

Overall, the most common adverse reactions in patients receiving a single 2-gram dose of azithromycin were related to the gastrointestinal system. Adverse reactions that occurred in patients in this study with a frequency of 1% or greater included nausea (18%), diarrhea/loose stools (14%), vomiting (7%), abdominal pain (7%), vaginitis (2%), dyspepsia (1%), and dizziness (1%). The majority of these complaints were mild in nature.

Pediatric Patients

Single and Multiple-dose regimens: The types of adverse reactions in pediatric patients were comparable to those seen in adults, with different incidence rates for the dosage regimens recommended in pediatric patients.

Acute Otitis Media: For the recommended total dosage regimen of 30 mg/kg, the most frequent adverse reactions (≥ 1%) attributed to treatment were diarrhea, abdominal pain, vomiting, nausea, and rash. [see Dosage and Administration (2) and Clinical Studies (14.2)]

The incidence, based on dosing regimen, is described in the table below:

Dosage Regimen Diarrhea % Abdominal Pain % Vomiting % Nausea % Rash %
1-day 4.3% 1.4% 4.9% 1.0% 1.0%
3-day 2.6% 1.7% 2.3% 0.4% 0.6%
5-day 1.8% 1.2% 1.1% 0.5% 0.4%

Community-Acquired Pneumonia: For the recommended dosage regimen of 10 mg/kg on Day 1 followed by 5 mg/kg on Days 2 to 5, the most frequent adverse reactions attributed to treatment were diarrhea/loose stools, abdominal pain, vomiting, nausea, and rash.

The incidence is described in the table below:

Dosage Regimen Diarrhea/Loose stools % Abdominal Pain % Vomiting % Nausea % Rash %
5-day 5.8 % 1.9 % 1.9 % 1.9 % 1.6%

Pharyngitis/Tonsillitis: For the recommended dosage regimen of 12 mg/kg on Days 1 to 5, the most frequent adverse reactions attributed to treatment were diarrhea, vomiting, abdominal pain, nausea, and headache.

The incidence is described in the table below:

Dosage Regimen Diarrhea % Abdominal Pain % Vomiting % Nausea % Rash % Headache %
5-day 5.4 % 3.4 % 5.6 % 1.8 % 0.7 % 1.1 %

With any of the treatment regimens, no other adverse reactions occurred in pediatric patients treated with azithromycin with a frequency greater than 1%. Adverse reactions that occurred with a frequency of 1% or less included the following:

Cardiovascular: Chest pain.
Gastrointestinal: Dyspepsia, constipation, anorexia, enteritis, flatulence, gastritis, jaundice, loose stools, and oral moniliasis.
Hematologic and Lymphatic: Anemia and leukopenia.
Nervous System: Headache (otitis media dosage), hyperkinesia, dizziness, agitation, nervousness, and insomnia.
General: Fever, face edema, fatigue, fungal infection, malaise, and pain.
Allergic: Rash and allergic reaction.
Respiratory: Cough, pharyngitis, pleural effusion, and rhinitis.
Skin and Appendages: Eczema, fungal dermatitis, pruritus, sweating, urticaria, and vesiculobullous rash.
Special Senses: Conjunctivitis.

6.2 Postmarketing Experience

The following adverse reactions have been identified during post-approval use of azithromycin. Because these reactions are reported voluntarily from a population of uncertain size, it is not always possible to reliably estimate their frequency or establish a causal relationship to drug exposure.

Adverse reactions reported with azithromycin during the postmarketing period in adult and/or pediatric patients for which a causal relationship may not be established include:

Allergic: Arthralgia, edema, urticaria, and angioedema.
Cardiovascular: Arrhythmias including ventricular tachycardia and hypotension. There have been reports of QT prolongation and torsades de pointes.
Gastrointestinal: Anorexia, constipation, dyspepsia, flatulence, vomiting/diarrhea, pseudomembranous colitis, pancreatitis, oral candidiasis, pyloric stenosis, and reports of tongue discoloration.
General: Asthenia, paresthesia, fatigue, malaise, and anaphylaxis.
Genitourinary: Interstitial nephritis, acute renal failure, and vaginitis.
Hematopoietic: Thrombocytopenia.
Liver/Biliary: Abnormal liver function, hepatitis, cholestatic jaundice, hepatic necrosis, and hepatic failure. [see Warnings and Precautions (5.2)]
Nervous System: Convulsions, dizziness/vertigo, headache, somnolence, hyperactivity, nervousness, agitation, and syncope.
Psychiatric: Aggressive reaction and anxiety.
Skin/Appendages: Pruritus serious skin reactions including erythema multiforme, AGEP, Stevens-Johnson Syndrome, toxic epidermal necrolysis, and DRESS.
Special Senses: Hearing disturbances including hearing loss, deafness and/or tinnitus, and reports of taste/smell perversion and/or loss.

6.3 Laboratory Abnormalities

Adults:

Clinically significant abnormalities (irrespective of drug relationship) occurring during the clinical trials were reported as follows: with an incidence of greater than 1%: decreased hemoglobin, hematocrit, lymphocytes, neutrophils, and blood glucose; elevated serum creatine phosphokinase, potassium, ALT, GGT, AST, BUN, creatinine, blood glucose, platelet count, lymphocytes, neutrophils, and eosinophils; with an incidence of less than 1%: leukopenia, neutropenia, decreased sodium, potassium, platelet count, elevated monocytes, basophils, bicarbonate, serum alkaline phosphatase, bilirubin, LDH, and phosphate. The majority of subjects with elevated serum creatinine also had abnormal values at baseline. When follow-up was provided, changes in laboratory tests appeared to be reversible.

In multiple-dose clinical trials involving more than 5,000 patients, four patients discontinued therapy because of treatment-related liver enzyme abnormalities and one because of a renal function abnormality.

Pediatric Patients:

One, Three, and Five Day Regimens

Laboratory data collected from comparative clinical trials employing two 3-day regimens (30 mg/kg or 60 mg/kg in divided doses over 3 days), or two 5-day regimens (30 mg/kg or 60 mg/kg in divided doses over 5 days) were similar for regimens of azithromycin and all comparators combined, with most clinically significant laboratory abnormalities occurring at incidences of 1% to 5%. Laboratory data for patients receiving 30 mg/kg as a single dose were collected in one single center trial. In that trial, an absolute neutrophil count between 500 cells/mm3 to 1,500 cells/mm3 was observed in 10/64 patients receiving 30 mg/kg as a single dose, 9/62 patients receiving 30 mg/kg given over 3 days, and 8/63 comparator patients. No patient had an absolute neutrophil count <500 cells/mm3.

In multiple-dose clinical trials involving approximately 4,700 pediatric patients, no patients discontinued therapy because of treatment-related laboratory abnormalities.

DRUG INTERACTIONS

7.1 Nelfinavir

Co-administration of nelfinavir at steady-state with a single oral dose of azithromycin resulted in increased azithromycin serum concentrations. Although a dose adjustment of azithromycin is not recommended when administered in combination with nelfinavir, close monitoring for known adverse reactions of azithromycin, such as liver enzyme abnormalities and hearing impairment, is warranted. [see Adverse Reactions (6)]

7.2 Warfarin

Spontaneous postmarketing reports suggest that concomitant administration of azithromycin may potentiate the effects of oral anticoagulants such as warfarin, although the prothrombin time was not affected in the dedicated drug interaction study with azithromycin and warfarin. Prothrombin times should be carefully monitored while patients are receiving azithromycin and oral anticoagulants concomitantly.

7.3 Potential Drug-Drug Interactions with Macrolides

Interactions with digoxin, colchicine or phenytoin have not been reported in clinical trials with azithromycin. No specific drug interaction studies have been performed to evaluate potential drug-drug interactions. However, drug interactions have been observed with other macrolide products. Until further data are developed regarding drug interactions when digoxin, colchicine or phenytoin are used with azithromycin careful monitoring of patients is advised.

USE IN SPECIFIC POPULATIONS

8.1 Pregnancy

Risk Summary

Available data from published literature and postmarketing experience over several decades with azithromycin use in pregnant women have not identified any drug-associated risks for major birth defects, miscarriage, or adverse maternal or fetal outcomes (see Data). Developmental toxicity studies with azithromycin in rats, mice, and rabbits showed no drug-induced fetal malformations at doses up to 4, 2, and 2 times, respectively, an adult human daily dose of 500 mg based on body surface area. Decreased viability and delayed development were observed in the offspring of pregnant rats administered azithromycin from day 6 of pregnancy through weaning at a dose equivalent to 4 times an adult human daily dose of 500 mg based on body surface area (see Data).

The estimated background risk of major birth defects and miscarriage for the indicated populations is unknown. All pregnancies have a background risk of birth defect, loss, or other adverse outcomes. In the U.S. general population, the estimated background risk of major birth defects and miscarriage in clinically recognized pregnancies is 2% to 4% and 15% to 20%, respectively.

Data

Human Data

Available data from published observational studies, case series, and case reports over several decades do not suggest an increased risk for major birth defects, miscarriage, or adverse maternal or fetal outcomes with azithromycin use in pregnant women. Limitations of these data include the lack of randomization and inability to control for confounders such as underlying maternal disease and maternal use of concomitant medications.

Animal Data

Azithromycin administered during the period of organogenesis did not cause fetal malformations in rats and mice at oral doses up to 200 mg/kg/day (moderately maternally toxic). Based on body surface area, this dose is approximately 4 (rats) and 2 (mice) times an adult human daily dose of 500 mg. In rabbits administered azithromycin at oral doses of 10 mg/kg/day, 20 mg/kg/day, and 40 mg/kg/day during organogenesis, reduced maternal body weight and food consumption were observed in all groups; no evidence of fetotoxicity or teratogenicity was observed at these doses, the highest of which is estimated to be 2 times an adult human daily dose of 500 mg based on body surface area.

In a pre- and postnatal development study, azithromycin was administered orally to pregnant rats from day 6 of pregnancy until weaning at doses of 50 mg/kg/day or 200 mg/kg/day. Maternal toxicity (reduced food consumption and body weight gain; increased stress at parturition) was observed at the higher dose. Effects in the offspring were noted at 200 mg/kg/day during the postnatal development period (decreased viability, delayed developmental landmarks). These effects were not observed in a pre- and postnatal rat study when up to 200 mg/kg/day of azithromycin was given orally beginning on day 15 of pregnancy until weaning.

8.2 Lactation

Risk Summary

Azithromycin is present in human milk (see Data). Non-serious adverse reactions have been reported in breastfed infants after maternal administration of azithromycin (see Clinical Considerations). There are no available data on the effects of azithromycin on milk production. The developmental and health benefits of breastfeeding should be considered along with the mother's clinical need for azithromycin and any potential adverse effects on the breastfed infant from azithromycin or from the underlying maternal condition.

Clinical Considerations

Advise women to monitor the breastfed infant for diarrhea, vomiting, or rash.

Data

Azithromycin breastmilk concentrations were measured in 20 women after receiving a single 2 g oral dose of azithromycin during labor. Breastmilk samples collected on days 3 and 6 postpartum as well as 2 and 4 weeks postpartum revealed the presence of azithromycin in breastmilk up to 4 weeks after dosing. In another study, a single dose of azithromycin 500 mg was administered intravenously to 8 women prior to incision for cesarean section. Breastmilk (colostrum) samples obtained between 12 and 48 hours after dosing revealed that azithromycin persisted in breastmilk up to 48 hours.

8.4 Pediatric Use

[see Clinical Pharmacology (12.3), Indications and Usage (1.2), and Dosage and Administration (2.2)]

Safety and effectiveness in the treatment of pediatric patients with acute otitis media, acute bacterial sinusitis and community-acquired pneumonia under 6 months of age have not been established. Use of azithromycin for the treatment of acute bacterial sinusitis and community-acquired pneumonia in pediatric patients (6 months of age or greater) is supported by adequate and well-controlled trials in adults.

Pharyngitis/Tonsillitis: Safety and effectiveness in the treatment of pediatric patients with pharyngitis/tonsillitis under 2 years of age have not been established.

8.5 Geriatric Use

In multiple-dose clinical trials of oral azithromycin, 9% of patients were at least 65 years of age (458/4,949) and 3% of patients (144/4,949) were at least 75 years of age. No overall differences in safety or effectiveness were observed between these subjects and younger subjects, and other reported clinical experience has not identified differences in response between the elderly and younger patients, but greater sensitivity of some older individuals cannot be ruled out.

Elderly patients may be more susceptible to development of torsades de pointes arrhythmias than younger patients. [see Warnings and Precautions (5.4)]

HOW SUPPLIED

Azithromycin Tablets USP, 500 mg are supplied as red, oval, film coated tablets containing azithromycin dihydrate equivalent to 500 mg of azithromycin.

Azithromycin Tablets USP, 500 mg are debossed "OE" on one side and "500" on the other side. These are packaged in bottles and blister cards of 3 tablets as follows:

Bottles of 30 tablets with child-resistant closure NDC 68094-799-30
Bottles of 100 tablets with child-resistant closure NDC 68094-799-50
Cartons of 1 blister card with child-resistant package (3 tablets per blister card) NDC 68094-799-03
Cartons of 3 blister cards with child-resistant package (3 tablets per blister card) NDC 68094-799-09

Store at 20° to 25°C (68° to 77°F); excursions permitted from 15° to 30°C (59° to 86°F) [see USP Controlled Room Temperature].

Dispense in tight containers (USP).

PATIENT COUNSELING INFORMATION

Advise the patient to read the FDA-approved patient labeling (Patient Information).

General Patient Counseling

Azithromycin tablets can be taken with or without food.

Patients should also be cautioned not to take aluminum- and magnesium-containing antacids and azithromycin simultaneously.

The patient should be directed to discontinue azithromycin immediately and contact a physician if any signs of an allergic reaction occur.

Direct parents or caregivers to contact their physician if vomiting and irritability with feeding occurs in the infant.

Patients should be counseled that antibacterial drugs including azithromycin should only be used to treat bacterial infections. They do not treat viral infections (e.g., the common cold). When azithromycin is prescribed to treat a bacterial infection, patients should be told that although it is common to feel better early in the course of the therapy, the medication should be taken exactly as directed. Skipping doses or not completing the full course of therapy may (1) decrease the effectiveness of the immediate treatment and (2) increase the likelihood that bacteria will develop resistance and will not be treatable by azithromycin or other antibacterial drugs in the future.

Diarrhea is a common problem caused by antibacterials which usually ends when the antibacterial is discontinued. Sometimes after starting treatment with antibacterials patients can develop watery and bloody stools (with or without stomach cramps and fever) even as late as two or more months after having taken the last dose of the antibacterial drug. If this occurs, patients should contact their physician as soon as possible.

See FDA-approved Patient Labeling